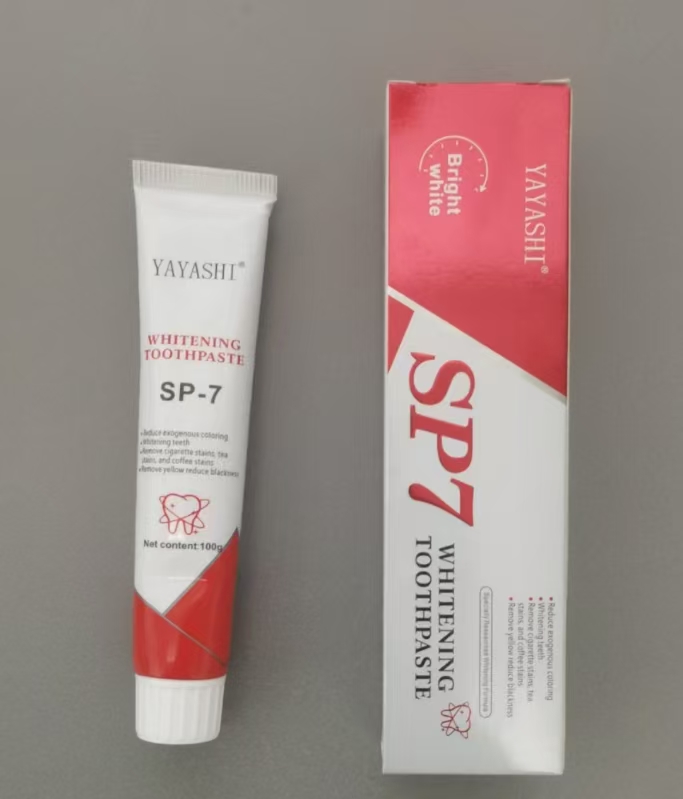 DRUG LABEL: Whitening
NDC: 84727-051 | Form: GEL, DENTIFRICE
Manufacturer: Guangzhou Baishili Trading Co., Ltd
Category: otc | Type: HUMAN OTC DRUG LABEL
Date: 20241112

ACTIVE INGREDIENTS: HYDRATED SILICA 0.5 g/0.5 g; GLYCERIN 0.5 g/0.5 g; XANTHAN GUM 0.5 g/0.5 g
INACTIVE INGREDIENTS: LYSOZYME 0.5 g/0.5 g; SODIUM PHYTATE 0.5 g/0.5 g; SORBITOL 0.5 g/0.5 g; WATER 0.5 g/0.5 g; SACCHARIN SODIUM 0.5 g/0.5 g; SODIUM LAURYL SULFATE 0.5 g/0.5 g

PURPOSE

Emphasize that the toothpaste uses mild whitening ingredients that do not damage tooth enamel, is suitable for daily use, and helps users easily achieve teeth whitening effects

Warnings:

For external use only: Do not ingest the toothpaste. If swallowed, seek medical help immediately.

Avoid use on damaged or sensitive gums: If you have sensitive teeth, gums, or any oral health concerns, consult with a dentist before using this product.

Possible sensitivity: Some individuals may experience mild tooth or gum sensitivity with whitening products. Discontinue use if sensitivity persists or worsens, and consult a dentist if necessary.

Keep out of reach of children: This product is intended for adults and should be stored out of reach of children. Children under 12 years of age should only use this product with the guidance of a dentist.

Avoid contact with eyes: In case of accidental contact with eyes, rinse thoroughly with water. Seek medical attention if irritation continues.

Example: "For external use only. Do not swallow. Consult a dentist if you have sensitive teeth or gums. Discontinue use if sensitivity occurs. Keep out of reach of children and avoid contact with eyes."

Indications:

This product is intended for individuals looking to remove surface stains and achieve a natural whitening effect.
Suitable for adults experiencing mild tooth discoloration caused by coffee, tea, red wine, or smoking.
Not recommended for individuals with sensitive teeth or gums. Please consult a dentist before use if you have dental concerns.

Usage:

Use twice daily, morning and night. Apply a pea-sized amount of toothpaste to your toothbrush.
Gently brush teeth for at least two minutes, ensuring the toothpaste covers all tooth surfaces.
Rinse thoroughly after brushing; avoid swallowing.
For optimal whitening results, continue use for at least two weeks, and limit consumption of stain-causing foods and drinks.

Stop Use:

If irritation or discomfort occurs: Discontinue use immediately if you experience persistent irritation, discomfort, or unusual sensitivity in teeth or gums.

If symptoms worsen: Stop using the product if symptoms such as pain, inflammation, or tooth sensitivity intensify. Consult a dentist before resuming use.

If allergic reaction develops: Discontinue use if you notice signs of an allergic reaction, such as redness, itching, or swelling in the mouth or on the gums.

KEEP OUT OF REACH OF CHILDREN

Here’s how the KEEP OUT OF REACH OF CHILDREN section could be presented for a whitening toothpaste:

Keep Out of Reach of Children:

This product is intended for adult use only. Do not allow children to use without supervision or the guidance of a dentist.

In case of accidental ingestion by a child, seek immediate medical assistance or contact a Poison Control Center.

Example: "Keep out of reach of children. For adult use only. If swallowed by a child, get medical help or contact a Poison Control Center immediately."

DOSAGE AND ADMINISTRATION

Here’s how the DOSAGE & ADMINISTRATION section for a whitening toothpaste could be structured:

Dosage & Administration:

Recommended Dosage: Use a pea-sized amount of toothpaste per brushing session.

Frequency of Use: Brush teeth twice daily, in the morning and at night, or as directed by a dentist.

Administration Instructions:

Apply a pea-sized amount of toothpaste to a toothbrush.
Brush teeth gently for at least two minutes, covering all tooth surfaces.
Rinse thoroughly after brushing and avoid swallowing the product.

Duration for Optimal Results: For best whitening results, use consistently for a minimum of two weeks. Consult a dentist if additional whitening is desired or if you plan to use for an extended period.

Example: "Apply a pea-sized amount and brush twice daily for two minutes, ensuring full coverage. Rinse thoroughly after use. For optimal whitening, continue use for at least two weeks."

INACTIVE INGREDIENT

LYSOZYME

SODIUM PHYTATE

SORBITOL

WATER

SACCHARIN SODIUM

SODIUM LAURYL SULFATE

DOSAGE AND ADMINISTRATION

HYDRATED SILICA

XANTHAN GUM

GLYCERIN